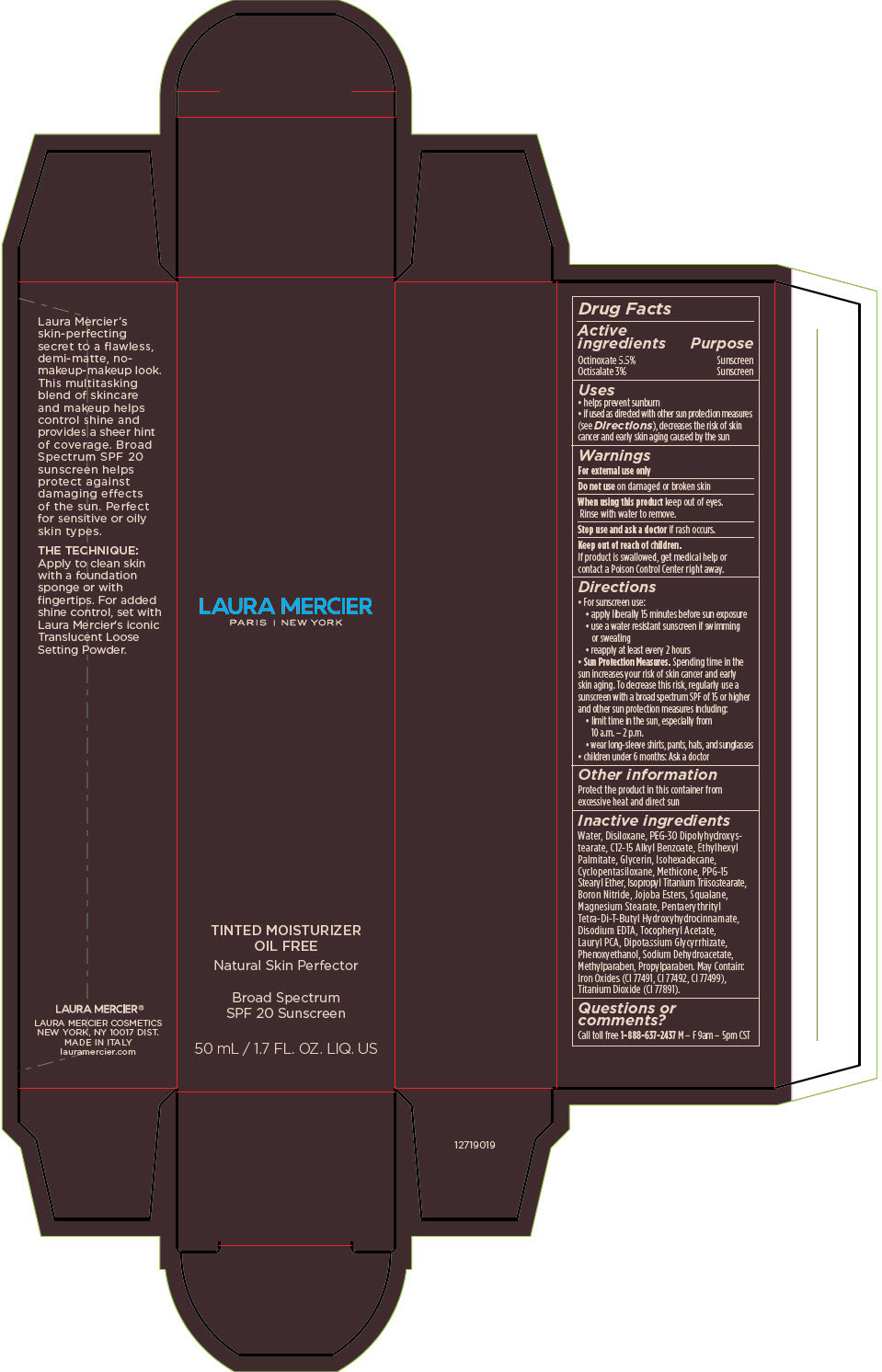 DRUG LABEL: Laura Mercier Tinted Moisturizer Oil Free Natural Skin Perfector Broad Spectrum SPF 20 Sunscreen
NDC: 82761-015 | Form: CREAM
Manufacturer: Laura Mercier US Buyer LLC
Category: otc | Type: HUMAN OTC DRUG LABEL
Date: 20231004

ACTIVE INGREDIENTS: OCTINOXATE 2.827 g/50 mL; OCTISALATE 1.542 g/50 mL
INACTIVE INGREDIENTS: WATER; HEXAMETHYLDISILOXANE; PEG-30 DIPOLYHYDROXYSTEARATE (4000 MW); ALKYL (C12-15) BENZOATE; ETHYLHEXYL PALMITATE; GLYCERIN; ISOHEXADECANE; CYCLOMETHICONE 5; METHICONE (20 CST); POLYPROPYLENE GLYCOL 15 STEARYL ETHER; ISOPROPYL TITANIUM TRIISOSTEARATE; BORON NITRIDE; SQUALANE; MAGNESIUM STEARATE; PENTAERYTHRITOL TETRAKIS(3-(3,5-DI-TERT-BUTYL-4-HYDROXYPHENYL)PROPIONATE); EDETATE DISODIUM; .ALPHA.-TOCOPHEROL ACETATE, DL-; LAURYL PIDOLATE; GLYCYRRHIZINATE DIPOTASSIUM; PHENOXYETHANOL; SODIUM DEHYDROACETATE; METHYLPARABEN; PROPYLPARABEN; FERRIC OXIDE RED; FERRIC OXIDE YELLOW; FERROSOFERRIC OXIDE; TITANIUM DIOXIDE

Laura Mercier Tinted Moisturizer Oil Free Natural Skin Perfector Broad Spectrum SPF 20 Sunscreen

Drug Facts

ACTIVE INGREDIENT

Active ingredients | Purpose
Octinoxate 5.5% | Sunscreen
Octisalate 3.0% | Sunscreen

Uses

- Helps prevent sunburn.

Warnings

For external use only

Do not use on damaged or broken skin

When using this product keep out of eyes. Rinse with water to remove.

Stop use and ask a doctor if rash occurs.

Keep out of reach of children. If product is swallowed, get medical help or contact a Poison Control Center right away.

Directions

- For sunscreen use:
  - apply liberally 15 minutes before sun exposure
  - Use a water resistant sunscreen if swimming or sweating.
  - Reapply at least every 2 hours.
- Sun Protection Measures. Spending time in the sun increases your risk of skin cancer and early skin aging. To decrease this risk, regularly use a sunscreen with a Broad Spectrum SPF of 15 or higher and other sun protection measures including:
  - limit time in the sun, especially from 10 a.m. – 2 p.m.
  - wear long-sleeve shirts, pants, hats, and sunglasses
  - children under 6 months: Ask a doctor

- Other information
  Protect this product in this container from excessive heat and direct sun

Inactive Ingredients

WATER, DISILOXANE, PEG-30 DIPOLYHYDROXYSTEARATE, C12-15 ALKYL BENZOATE, ETHYLHEXYL PALMITATE, GLYCERIN, ISOHEXADECANE, CYCLOPENTASILOXANE, METHICONE, PPG-15 STEARYL ETHER, ISOPROPYL TITANIUM TRIISOSTEARATE, BORON NITRIDE, JOJOBA ESTERS, SQUALANE, MAGNESIUM STEARATE, PENTAERYTHRITYL TETRA-DI-T-BUTYL HYDROXYHYDROCINNAMATE, DISODIUM EDTA, TOCOPHERYL ACETATE, LAURYL PCA, DIPOTASSIUM GLYCYRRHIZATE, PHENOXYETHANOL, SODIUM DEHYDROACETATE, METHYLPARABEN, PROPYLPARABEN. MAY CONTAIN: IRON OXIDES, TITANIUM DIOXIDE.

Questions or comments?

Call toll free 1-888-637-2437 M-F 9am – 5pm CST

PRINCIPAL DISPLAY PANEL - 50 mL Tube Carton - 0N1 Petal

LAURA MERCIER
PARIS | NEW YORK

TINTED MOISTURIZER
OIL FREE
Natural Skin Perfector

Broad Spectrum
SPF 20 Sunscreen

50 mL / 1.7 FL. OZ. LIQ. US

PRINCIPAL DISPLAY PANEL - 50 mL Tube Carton - 0W1 Pearl

LAURA MERCIER
PARIS | NEW YORK

TINTED MOISTURIZER
OIL FREE
Natural Skin Perfector

Broad Spectrum
SPF 20 Sunscreen

50 mL / 1.7 FL. OZ. LIQ. US

PRINCIPAL DISPLAY PANEL - 50 mL Tube Carton - 1C0 Cameo

LAURA MERCIER
PARIS | NEW YORK

TINTED MOISTURIZER
OIL FREE
Natural Skin Perfector

Broad Spectrum
SPF 20 Sunscreen

50 mL / 1.7 FL. OZ. LIQ. US

PRINCIPAL DISPLAY PANEL - 50 mL Tube Carton - 1N2 Vanille

LAURA MERCIER
PARIS | NEW YORK

TINTED MOISTURIZER
OIL FREE
Natural Skin Perfector

Broad Spectrum
SPF 20 Sunscreen

50 mL / 1.7 FL. OZ. LIQ. US

PRINCIPAL DISPLAY PANEL - 50 mL Tube Carton - 1W1 Porcelain

LAURA MERCIER
PARIS | NEW YORK

TINTED MOISTURIZER
OIL FREE
Natural Skin Perfector

Broad Spectrum
SPF 20 Sunscreen

50 mL / 1.7 FL. OZ. LIQ. US

PRINCIPAL DISPLAY PANEL - 50 mL Tube Carton - 2C1 Blush

LAURA MERCIER
PARIS | NEW YORK

TINTED MOISTURIZER
OIL FREE
Natural Skin Perfector

Broad Spectrum
SPF 20 Sunscreen

50 mL / 1.7 FL. OZ. LIQ. US

PRINCIPAL DISPLAY PANEL - 50 mL Tube Carton - 2N1 Nude

LAURA MERCIER
PARIS | NEW YORK

TINTED MOISTURIZER
OIL FREE
Natural Skin Perfector

Broad Spectrum
SPF 20 Sunscreen

50 mL / 1.7 FL. OZ. LIQ. US

PRINCIPAL DISPLAY PANEL - 50 mL Tube Carton - 2W1 Natural

LAURA MERCIER
PARIS | NEW YORK

TINTED MOISTURIZER
OIL FREE
Natural Skin Perfector

Broad Spectrum
SPF 20 Sunscreen

50 mL / 1.7 FL. OZ. LIQ. US

PRINCIPAL DISPLAY PANEL - 50 mL Tube Carton - 3C1 Fawn

LAURA MERCIER
PARIS | NEW YORK

TINTED MOISTURIZER
OIL FREE
Natural Skin Perfector

Broad Spectrum
SPF 20 Sunscreen

50 mL / 1.7 FL. OZ. LIQ. US

PRINCIPAL DISPLAY PANEL - 50 mL Tube Carton - 3N1 Sand

LAURA MERCIER
PARIS | NEW YORK

TINTED MOISTURIZER
OIL FREE
Natural Skin Perfector

Broad Spectrum
SPF 20 Sunscreen

50 mL / 1.7 FL. OZ. LIQ. US

PRINCIPAL DISPLAY PANEL - 50 mL Tube Carton - 3W1 Bisque

LAURA MERCIER
PARIS | NEW YORK

TINTED MOISTURIZER
OIL FREE
Natural Skin Perfector

Broad Spectrum
SPF 20 Sunscreen

50 mL / 1.7 FL. OZ. LIQ. US

PRINCIPAL DISPLAY PANEL - 50 mL Tube Carton - 4C1 Almond

LAURA MERCIER
PARIS | NEW YORK

TINTED MOISTURIZER
OIL FREE
Natural Skin Perfector

Broad Spectrum
SPF 20 Sunscreen

50 mL / 1.7 FL. OZ. LIQ. US

PRINCIPAL DISPLAY PANEL - 50 mL Tube Carton - 4N1 Wheat

LAURA MERCIER
PARIS | NEW YORK

TINTED MOISTURIZER
OIL FREE
Natural Skin Perfector

Broad Spectrum
SPF 20 Sunscreen

50 mL / 1.7 FL. OZ. LIQ. US

PRINCIPAL DISPLAY PANEL - 50 mL Tube Carton - 4W1 Tawny

LAURA MERCIER
PARIS | NEW YORK

TINTED MOISTURIZER
OIL FREE
Natural Skin Perfector

Broad Spectrum
SPF 20 Sunscreen

50 mL / 1.7 FL. OZ. LIQ. US

PRINCIPAL DISPLAY PANEL - 50 mL Tube Carton - 5C1 Nutmeg

LAURA MERCIER
PARIS | NEW YORK

TINTED MOISTURIZER
OIL FREE
Natural Skin Perfector

Broad Spectrum
SPF 20 Sunscreen

50 mL / 1.7 FL. OZ. LIQ. US

PRINCIPAL DISPLAY PANEL - 50 mL Tube Carton - 5N1 Walnut

LAURA MERCIER
PARIS | NEW YORK

TINTED MOISTURIZER
OIL FREE
Natural Skin Perfector

Broad Spectrum
SPF 20 Sunscreen

50 mL / 1.7 FL. OZ. LIQ. US

PRINCIPAL DISPLAY PANEL - 50 mL Tube Carton - 5W1 Tan

LAURA MERCIER
PARIS | NEW YORK

TINTED MOISTURIZER
OIL FREE
Natural Skin Perfector

Broad Spectrum
SPF 20 Sunscreen

50 mL / 1.7 FL. OZ. LIQ. US

PRINCIPAL DISPLAY PANEL - 50 mL Tube Carton - 6C1 Cacao

LAURA MERCIER
PARIS | NEW YORK

TINTED MOISTURIZER
OIL FREE
Natural Skin Perfector

Broad Spectrum
SPF 20 Sunscreen

50 mL / 1.7 FL. OZ. LIQ. US

PRINCIPAL DISPLAY PANEL - 50 mL Tube Carton - 6N1 Mocha

LAURA MERCIER
PARIS | NEW YORK

TINTED MOISTURIZER
OIL FREE
Natural Skin Perfector

Broad Spectrum
SPF 20 Sunscreen

50 mL / 1.7 FL. OZ. LIQ. US

PRINCIPAL DISPLAY PANEL - 50 mL Tube Carton - 6W1 Ganache

LAURA MERCIER
PARIS | NEW YORK

TINTED MOISTURIZER
OIL FREE
Natural Skin Perfector

Broad Spectrum
SPF 20 Sunscreen

50 mL / 1.7 FL. OZ. LIQ. US